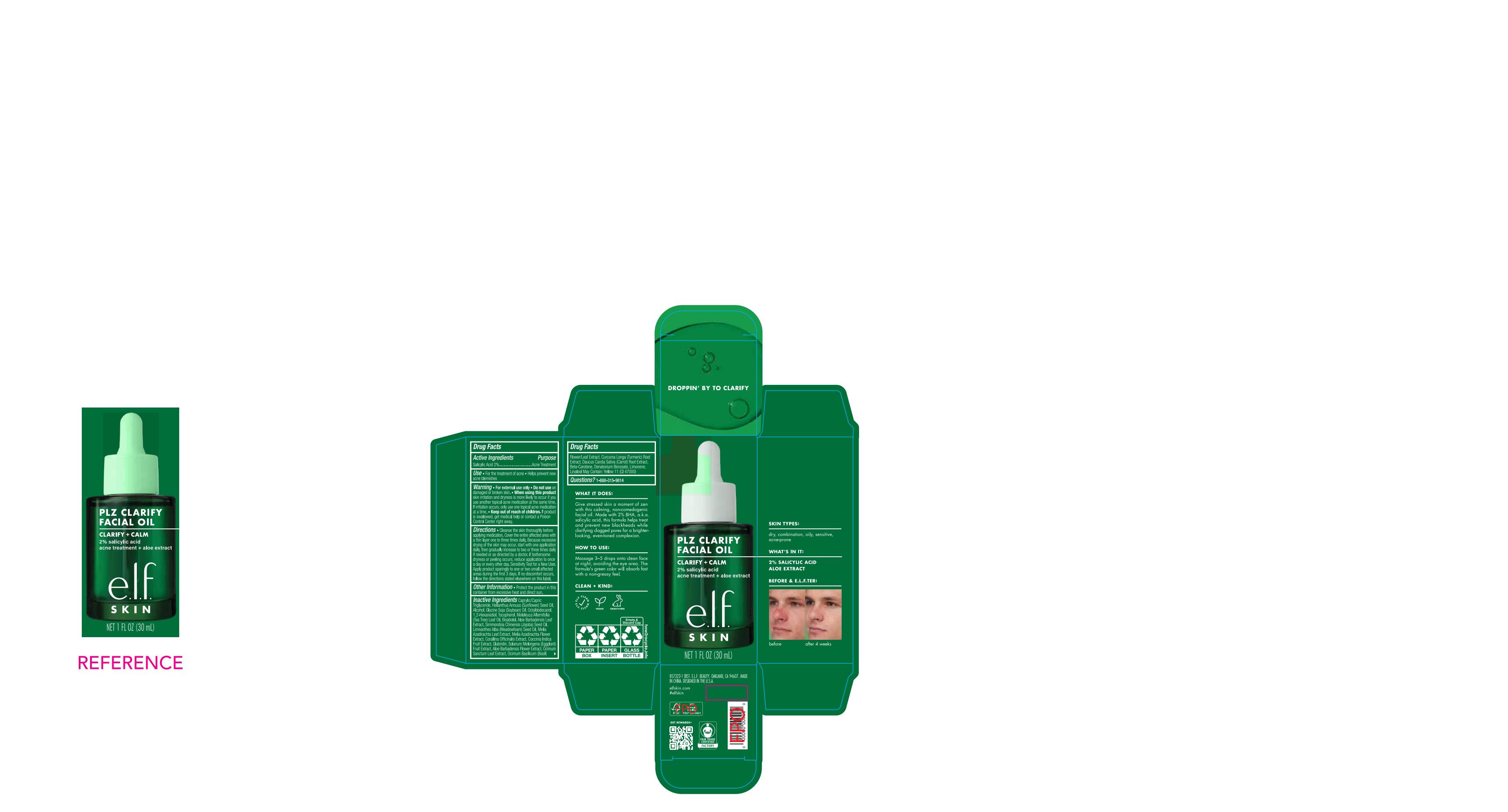 DRUG LABEL: e.l.f Plz Clarify Facial Oil
NDC: 70412-401 | Form: LIQUID
Manufacturer: Zhejiang Ayan Biotech Co., Ltd.
Category: otc | Type: HUMAN OTC DRUG LABEL
Date: 20241114

ACTIVE INGREDIENTS: SALICYLIC ACID 2 g/100 mL
INACTIVE INGREDIENTS: BISABOLOL; GLYCINE SOJA (SOYBEAN) OIL; COCCINIA INDICA FRUIT EXTRACT; ALOE BARBADENSIS LEAF EXTRACT; GLABRIDIN; CURCUMA LONGA (TURMERIC) ROOT EXTRACT; HELIANTHUS ANNUUS (SUNFLOWER) SEED OIL; CORALLINA OFFICINALIS EXTRACT; ALCOHOL; OCTYLDODECANOL; 1,2-HEXANEDIOL; OCIMUM BASILICUM (BASIL) FLOWER/LEAF EXTRACT; SIMMONDSIA CHINENSIS (JOJOBA) SEED OIL; DENATONIUM BENZOATE; CAPRYLIC/CAPRIC TRIGLYCERIDE; ALOE BARBADENSIS FLOWER EXTRACT; TOCOPHEROL; MELALEUCA ALTERNIFOLIA (TEA TREE) LEAF OIL; BETA-CAROTENE; LIMNANTHES ALBA (MEADOWFOAM) SEED OIL

Active Ingredients

Salgylic Arid 2%

Purpose

Acne Treatment

Warnings

·For external use only

Questions?

Questions?1-888-315-9814

Other Information

·Protect the product in thiscontainer from excessive heat and direct sun.

HOW TO USE:

Massage 3-5 drops onto clean faceat night,avoiding the eye area.Theformula's green color will absorb fastwith a non-greasy feel.

Inactive Ingredients

Caprylic/CapricTriglyceride,Heianthus Annuus (Sunflower) Seed Oil Alcohol,Glycine Soja (Soybean)Oil,Octyldodecanol,
1,2-Hexanediol,Tocopherol,Melaleuca Altermifolia(Tea Tree)Leaf 0i,Bisabolol,Aloe Barbadensis Leaf Extract,Simmondsia Chinensis (Jojoba)Seed Oil,Limnanthes Alba(Meadowfoam)Seed Oil,Melia Azadirachta Leaf Extract,Melia Azadirachta Flower Extract,Corallina Officinalis Extract,Coccinia Indica Fuit Extact,Gabridn,Solanum Melongena (Eggplant)Fruit Extract,Aloe Barbadensis Fower Etract,Ocimum Sanctum Leaf Extract,Ocimum Baslicum(Basil) Flower/Leaf Extract,Curcuma Longa (Turmeric) Root Extract,Daucus Carota Sativa(Carrot) Root Extract,Beta-Carotene,Denatonium Benzoate,Limonene,Linalool May Contain:Yellow 11(Cl 47000)

Use

·For the treatment of acne

·Helps prevent newacne blemishes

WHAT IT DOES:

Give stressed skin a moment of zen with this calming,non- comedogenic facial oil.Made with 2%BHA,a.k.a. salicylic acid,this formula helps treat and prevent new blackheads while clarifying clogged pores for a brighter-looking,even-toned complexion.

SKIN TYPES:

dry,combination,oily,sensitive,acne-prone

Directions

·Cleanse the skin thoroughy before applying medication.Cover the entire affected area wiha thin layer one to three times daily.Because excessivedrying of the skin may occu,start with one applicationdaly,then gradualy increase to two or three times dalyif neededor as directed by a doctor If bothersome dryness or peeling occurs,reduce application to once a day or every other day.Sensitivity Test for a New User.Apply product sparingly to one or twosmall affected areas during the first 3 days If no discomfort occurs,follow the directions stated elsewhere on this label.

·Do not use on damaged or broken skin.

Keep out of reach of children

If productis swallowed,get medical help or contact a Poison Control Center right away.

When using this product

skin iritation and dyness is more likely to occur if you use another topical acne medication at the same time.f iritation occurs,only use one topical acne medication at a time.

PRINCIPAL DISPLAY PANEL

PLZ CLARIFY
FACIAL OIL
CLARIFY+CALM
2%salicylic acid
acne treatment+aloe extract
e.l.f
S KI N
NET 1FL 0Z (30mL)